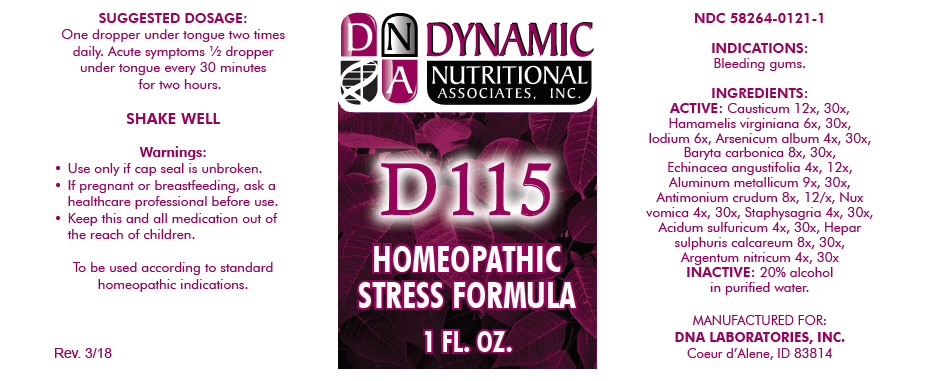 DRUG LABEL: D-115
NDC: 58264-0121 | Form: SOLUTION
Manufacturer: DNA Labs, Inc.
Category: homeopathic | Type: HUMAN OTC DRUG LABEL
Date: 20250113

ACTIVE INGREDIENTS: CAUSTICUM 12 [hp_X]/1 mL; HAMAMELIS VIRGINIANA ROOT BARK/STEM BARK 6 [hp_X]/1 mL; IODINE 6 [hp_X]/1 mL; ARSENIC TRIOXIDE 4 [hp_X]/1 mL; BARIUM CARBONATE 8 [hp_X]/1 mL; ECHINACEA ANGUSTIFOLIA 4 [hp_X]/1 mL; ALUMINUM 9 [hp_X]/1 mL; ANTIMONY TRISULFIDE 8 [hp_X]/1 mL; STRYCHNOS NUX-VOMICA SEED 4 [hp_X]/1 mL; DELPHINIUM STAPHISAGRIA SEED 4 [hp_X]/1 mL; SULFURIC ACID 4 [hp_X]/1 mL; CALCIUM SULFIDE 8 [hp_X]/1 mL; SILVER NITRATE 4 [hp_X]/1 mL
INACTIVE INGREDIENTS: ALCOHOL; WATER

D-115

NDC 58264-0121-1

INDICATIONS

PURPOSE

Bleeding gums.

INGREDIENTS

ACTIVE

Causticum 12x, 30x, Hamamelis virginiana 6x, 30x, Iodium 6x, Arsenicum album 4x, 30x, Baryta carbonica 8x, 30x, Echinacea angustifolia 4x, 12x, Aluminum metallicum 9x, 30x, Antimonium crudum 8x, 12/x, Nux vomica 4x, 30x, Staphysagria 4x, 30x, Acidum sulfuricum 4x, 30x, Hepar sulphuris calcareum 8x, 30x, Argentum nitricum 4x, 30x

INACTIVE

20% alcohol in purified water.

SUGGESTED DOSAGE

One dropper under tongue two times daily. Acute symptoms ½ dropper under tongue every 30 minutes for two hours.

STORAGE AND HANDLING

SHAKE WELL

Warnings

- Use only if cap seal is unbroken.

PREGNANCY OR BREAST FEEDING

- If pregnant or breastfeeding, ask a healthcare professional before use.

KEEP OUT OF REACH OF CHILDREN

- Keep this and all medication out of the reach of children.

To be used according to standard homeopathic indications.

PRINCIPAL DISPLAY PANEL - 1 FL. OZ. Bottle Label

DYNAMIC
NUTRITIONAL
ASSOCIATES, INC.

D 115

HOMEOPATHIC
STRESS FORMULA

1 FL. OZ.